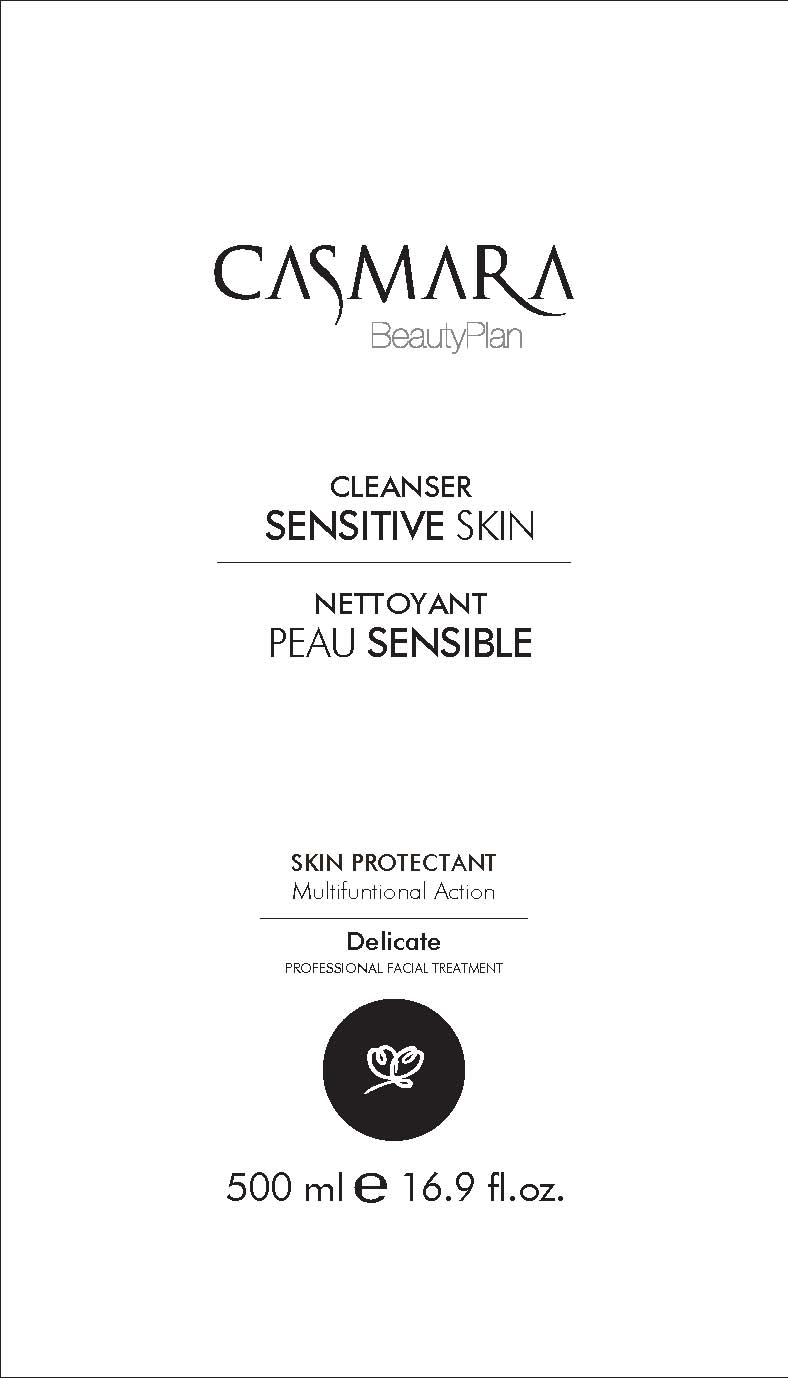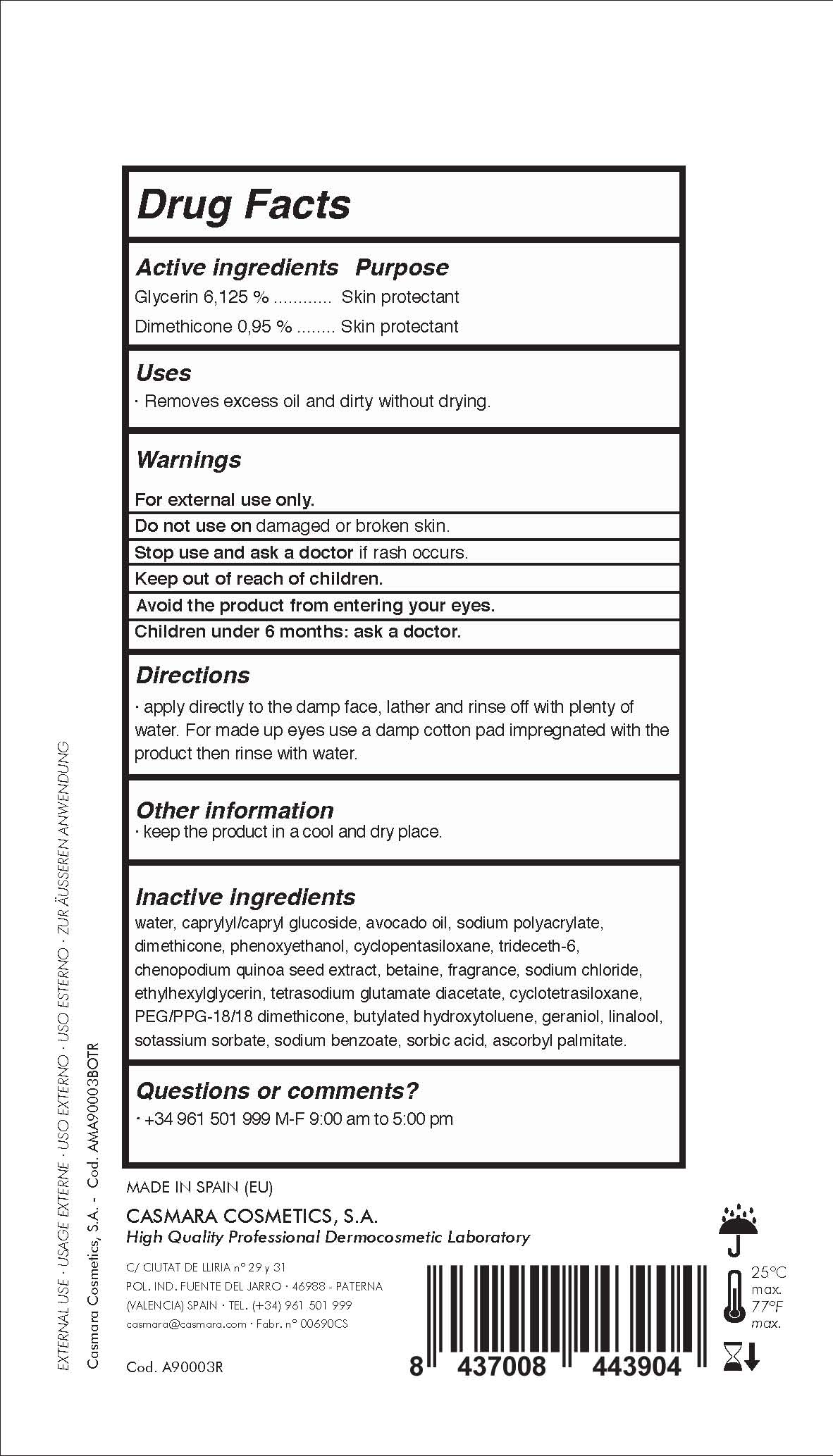 DRUG LABEL: Cleanser Sensitive Skin
NDC: 20151-072 | Form: LIQUID
Manufacturer: Casmara Cosmetics, SA
Category: otc | Type: HUMAN OTC DRUG LABEL
Date: 20161101

ACTIVE INGREDIENTS: DIMETHICONE 0.95 mg/1 mL; GLYCERIN 6.125 mg/1 mL
INACTIVE INGREDIENTS: CHENOPODIUM QUINOA SEED 0.225 mg/1 mL; ASCORBYL PALMITATE 0.0008 mg/1 mL; BUTYLATED HYDROXYTOLUENE 0.02 mg/1 mL; SORBIC ACID 0.003 mg/1 mL; POTASSIUM SORBATE 0.009 mg/1 mL; GERANIOL 0.02 mg/1 mL; AVOCADO OIL 2 mg/1 mL; ETHYLHEXYLGLYCERIN 0.1 mg/1 mL; WATER 86.883 mg/1 mL; PHENOXYETHANOL 0.9 mg/1 mL; TETRASODIUM GLUTAMATE DIACETATE 0.094 mg/1 mL; SODIUM POLYACRYLATE (8000 MW) 1.3 mg/1 mL; PERFLUNAFENE 0.2 mg/1 mL; CYCLOMETHICONE 4 0.05 mg/1 mL; CYCLOMETHICONE 5 0.45 mg/1 mL; TRIDECETH-6 0.3 mg/1 mL; SODIUM CHLORIDE 0.1 mg/1 mL; BETAINE 0.2 mg/1 mL; PEG/PPG-18/18 DIMETHICONE 0.05 mg/1 mL; SODIUM BENZOATE 0.006 mg/1 mL; LINALOOL, (+)- 0.014 mg/1 mL; CAPRYLYL GLUCOSIDE 6 mg/1 mL

Cleanser Sensitive Skin. Skin Protectant Multifuntional Action

WARNINGS

For external use only.

Do not use on damaged or broken skin.

Stop use and ask a doctor if rash occurs.

Keep out of reach of children.

Avoid the product from entering your eyes.

Children under 6 months: as a doctor.

Stop use and ask a doctor if rash occurs

Children under 6 months: ask a doctor

. keep out of reach of children

Questions or comments? + 34 961 501 099 M-F 9:00 am to 5:00 pm

OTHER SAFETY INFORMATION

. keep the product in a cool and dry place

Directions

. apply directly to the damp face, lather and rinse off with plenty of water.

. for made up eyes use a damp cotton pad impregnated with the product, then rinse with water

DOSAGE AND ADMINISTRATION

. apply directly to the damp face, lather and rinse off with plenty of water.

. for made up eyes use a damp cotton pad impregnated with the product, then rinse with water

Uses

. removes excess oil and dirty without drying

PURPOSE

. removes excess oil and dirty without drying.

Active Ingredients

Glycerin 6,12%........................... Skin Protectant

Dimethicone 0,95%.....................Skin Protectant

INACTIVE INGREDIENT

water, capryl glucoside, avocado oil, sodium polyacrylate, phenoxyethanol, cyclopentasiloxane, trideceth-6, chenopodium quinoa seed extract, betaine, fragrance, sodium chloride, ethylhexylglycerin, tetrasodium glutamate diacetate, cyclotetrasiloxane, PEG/PPG-18/18 dimethicone, butylated hydroxytoluene, geraniol, linalool,postasium sorbate, sodium benzoate, sorbic acid, ascorbyl palmitate.

PACKAGE LABEL

Cleanser Sensitive Skin

Skin protectant

Multifuntional action

Delicate

Facial Collection